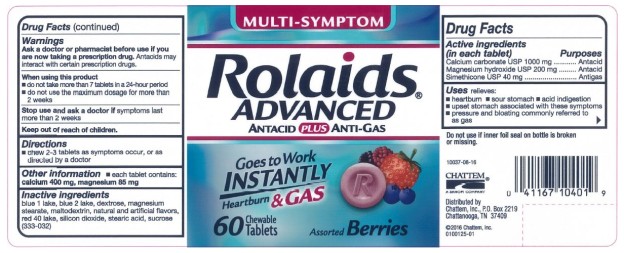 DRUG LABEL: Rolaids Advanced Antacid Anti-gas Mixed Berry
NDC: 41167-1040 | Form: TABLET, CHEWABLE
Manufacturer: Chattem, Inc.
Category: otc | Type: HUMAN OTC DRUG LABEL
Date: 20250410

ACTIVE INGREDIENTS: CALCIUM CARBONATE 1000 mg/1 1; MAGNESIUM HYDROXIDE 200 mg/1 1; DIMETHICONE 40 mg/1 1
INACTIVE INGREDIENTS: FD&C BLUE NO. 1; FD&C BLUE NO. 2; DEXTROSE; MAGNESIUM STEARATE; MALTODEXTRIN; FD&C RED NO. 40; SILICON DIOXIDE; STEARIC ACID; SUCROSE

Rolaids Advanced Antacid

MULTI-SYMPTOM Rolaids ADVANCED ANTACID PLUS ANTI-GAS

Drug Facts

Active ingredients

(in each tablet)
Calcium carbonate USP 1000 mg
Magnesium hydroxide USP 200 mg
Simethicone USP 40 mg

Purpose

Antacid
Antacid
Antigas

Use

relieves:

- heartburn
- sour stomach
- acid indigestion
- upset stomach associated with these symptoms
- pressure and bloating commonly referred to as gas

Warnings

Ask a doctor or pharmacist before use if you are

now taking a prescription drug. Antacids may interact with certain prescription drugs.

When using this product

- do not take more than 7 tablets in a 24-hour period
- do not use the maximum dosage for more than 2 weeks

Directions

- chew 2-3 tablets as symptoms occur, or as directed by a doctor

Other information

- each tablet contains: calcium 400 mg, magnesium 85 mg

Inactive ingredients

blue 1 lake, blue 2 lake, dextrose, magnesium stearate, maltodextrin, natural and artificial flavors, red 40 lake, silicon dioxide, stearic acid, sucralose, sucrose (309-145)

PRINCIPAL DISPLAY PANEL

MULTI-SYMPTOM
Rolaids®
ADVANCED
ANTACID PLUS ANTI-GAS
60 Chewable Tablets
Mixed Berries